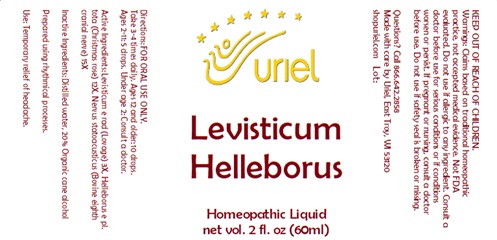 DRUG LABEL: Levisticum Helleborus
NDC: 48951-6092 | Form: LIQUID
Manufacturer: Uriel Pharmacy, Inc.
Category: homeopathic | Type: HUMAN OTC DRUG LABEL
Date: 20241220

ACTIVE INGREDIENTS: HELLEBORUS FOETIDUS ROOT 12 [hp_X]/1 mL; BOS TAURUS NERVE 15 [hp_X]/1 mL; LEVISTICUM OFFICINALE ROOT 3 [hp_X]/1 mL
INACTIVE INGREDIENTS: ALCOHOL; WATER

Levisticum Helleborus

INDICATIONS AND USAGE

Directions: FOR ORAL USE ONLY.

DOSAGE AND ADMINISTRATION

Take 3-4 times daily. Ages 12 and older: 10 drops.
Ages 2-11: 5 drops. Under age 2: Consult a doctor.

ACTIVE INGREDIENT

Active Ingredients: Levisticum e rad (Lovage) 3X, Helleborus e pl. tota (Christmas rose) 12X, Nervus statoacusticus (Bovine eighth cranial nerve) 15X

Inactive Ingredients: Distilled water, 20% Organic cane alcohol

Prepared using rhythmical processes.

PURPOSE

Use: Temporary relief of headache.

KEEP OUT OF REACH OF CHILDREN.

WARNINGS

Warnings: Claims based on traditional homeopathic practice, not accepted medical evidence. Not FDA evaluated. Do not use if allergic to any ingredient. Consult a doctor before use for serious conditions or if conditions worsen or persist. If pregnant or nursing, consult a doctor before use. Do not use if safety seal is broken or missing.

Questions? Call 866.642.2858
Made with care by Uriel, East Troy, WI 53120
shopuriel.com Lot: